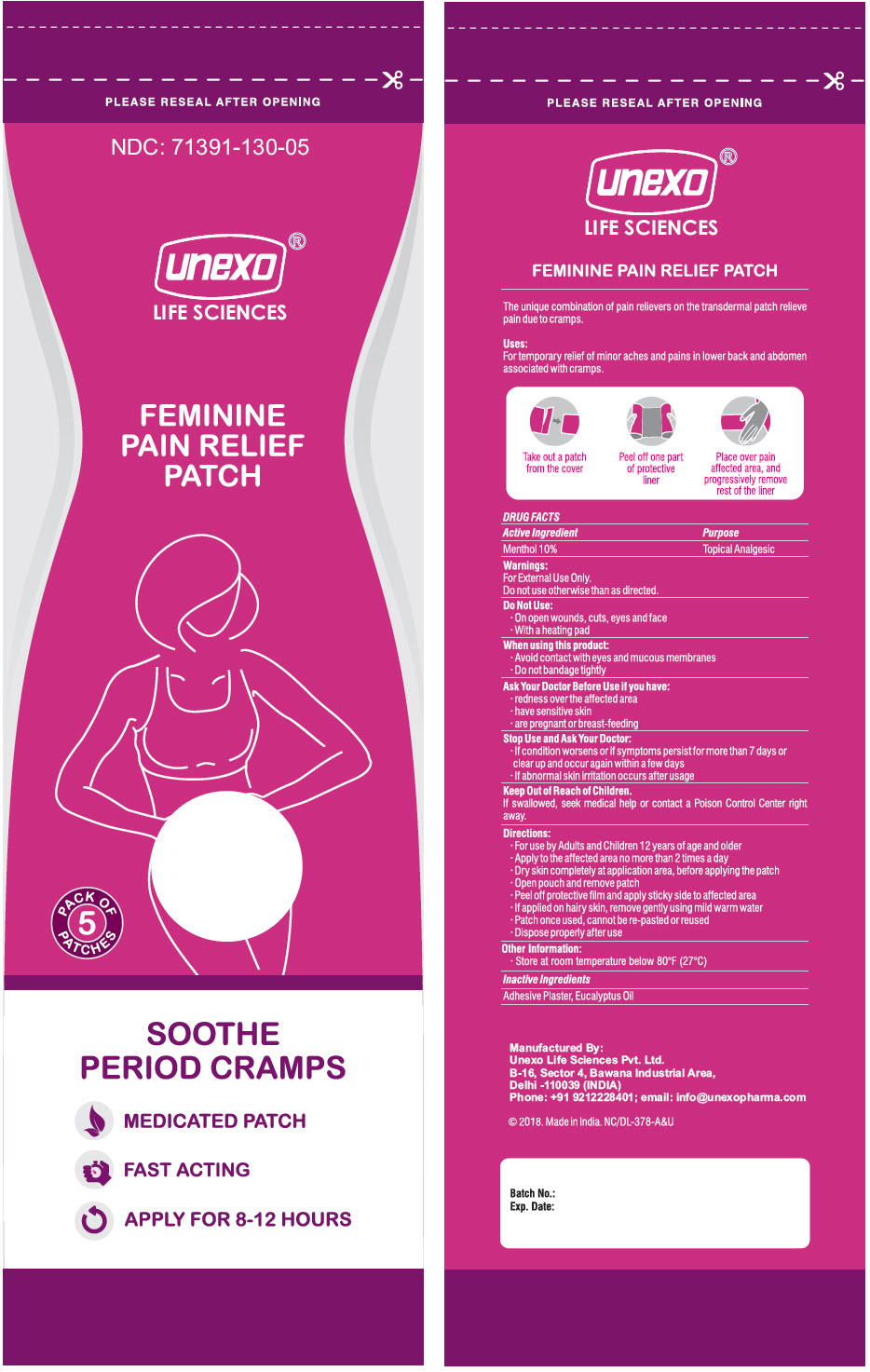 DRUG LABEL: FEMININE PAIN RELIEF
NDC: 71391-130 | Form: PATCH
Manufacturer: Unexo Life Sciences, Private Limited
Category: otc | Type: HUMAN OTC DRUG LABEL
Date: 20250113

ACTIVE INGREDIENTS: MENTHOL, UNSPECIFIED FORM 200 mg/1 1
INACTIVE INGREDIENTS: Eucalyptus Oil

FEMININE PAIN RELIEF

DRUG FACTS

Uses

For temporary relief of minor aches and pains in lower back and abdomen associated with cramps.

Active Ingredient

Menthol 10%

Purpose

Topical Analgesic

Warnings

For External Use Only.

Do not use otherwise than as directed.

Do Not Use

- On open wounds, cuts, eyes and face
- With a heating pad

When using this product

- Avoid contact with eyes and mucous membranes
- Do not bandage tightly

Ask Your Doctor Before Use if you have

- redness over the affected area
- have sensitive skin
- are pregnant or breast-feeding

Stop Use and Ask Your Doctor

- If condition worsens or if symptoms persist for more than 7 days or clear up and occur again within a few days
- If abnormal skin irritation occurs after usage

Keep Out of Reach of Children.

If swallowed, seek medical help or contact a Poison Control Center right away.

Directions

- For use by Adults and Children 12 years of age and older
- Apply to the affected area no more than 2 times a day
- Dry skin completely at application area, before applying the patch
- Open pouch and remove patch
- Peel off protective film and apply sticky side to affected area
- If applied on hairy skin, remove gently using mild warm water
- Patch once used, cannot be re-pasted or reused
- Dispose properly after use

Other Information

- Store at room temperature below 80°F (27°C)

Inactive Ingredients

Adhesive Plaster, Eucalyptus Oil

Manufactured By:
Unexo Life Sciences Pvt. Ltd.
B-16, Sector 4, Bawana Industrial Area,
Delhi -110039 (INDIA)

PRINCIPAL DISPLAY PANEL - 5 Patch Pouch

PLEASE RESEAL AFTER OPENING

NDC: 71391-130-05

unexo®
LIFE SCIENCES

FEMININE
PAIN RELIEF
PATCH

PACK OF
5
PATCHES

SOOTHE
PERIOD CRAMPS

MEDICATED PATCH
FAST ACTING
APPLY FOR 8-12 HOURS